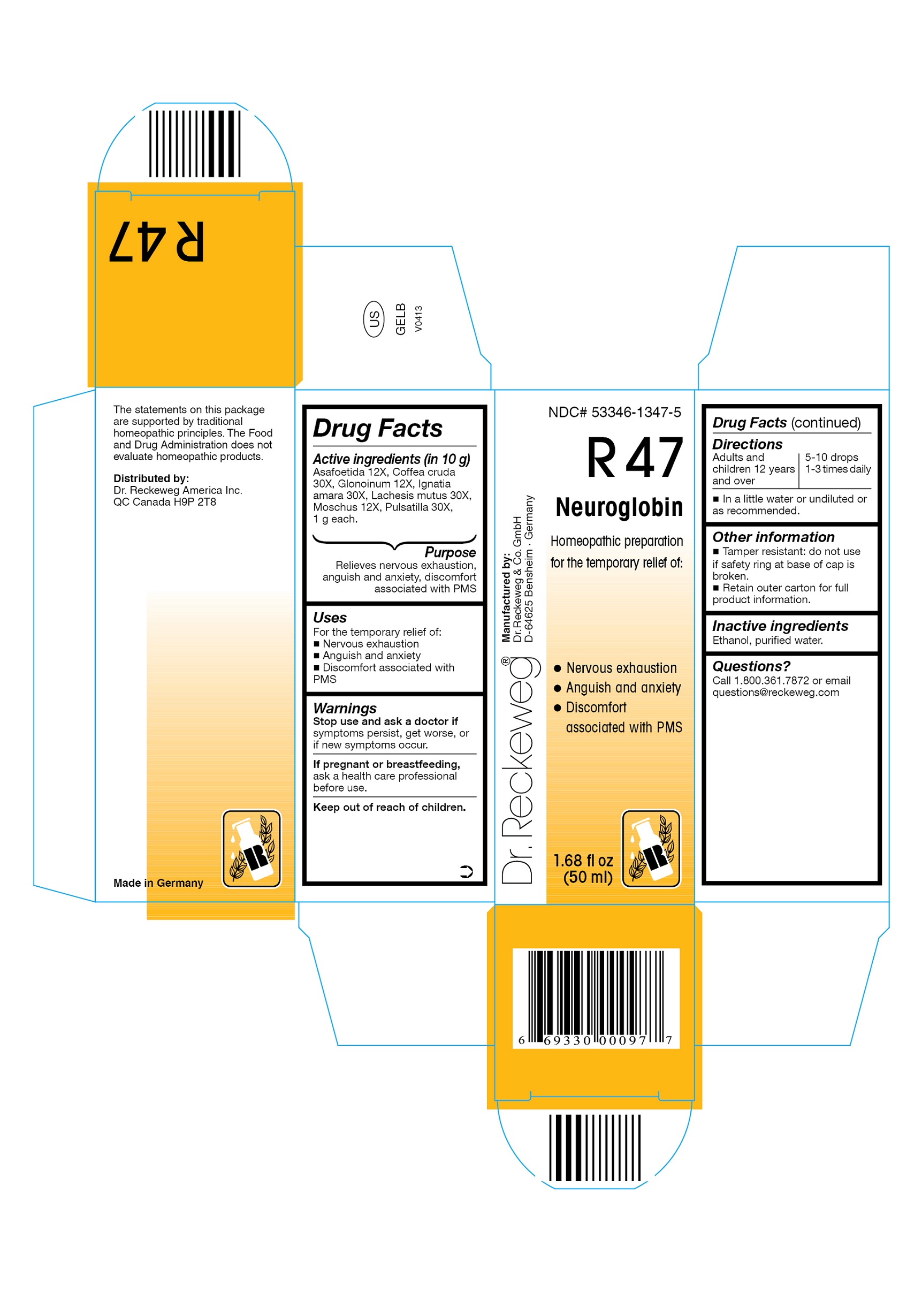 DRUG LABEL: DR. RECKEWEG R47 Neuroglobin
NDC: 53346-1347 | Form: LIQUID
Manufacturer: PHARMAZEUTISCHE FABRIK DR. RECKEWEG & CO
Category: homeopathic | Type: HUMAN OTC DRUG LABEL
Date: 20130405

ACTIVE INGREDIENTS: ASAFETIDA 12 [hp_X]/50 mL; ARABICA COFFEE BEAN 30 [hp_X]/50 mL; NITROGLYCERIN 12 [hp_X]/50 mL; STRYCHNOS IGNATII SEED 30 [hp_X]/50 mL; LACHESIS MUTA VENOM 30 [hp_X]/50 mL; MOSCHUS MOSCHIFERUS MUSK SAC RESIN 12 [hp_X]/50 mL; PULSATILLA PRATENSIS 30 [hp_X]/50 mL
INACTIVE INGREDIENTS: ALCOHOL; WATER

DR. RECKEWEG R47 Neuroglobin

Active ingredients

Asafoetida 12X, Coffea cruda 30X, Glonoinum 12X, Ignatia amara 30X, Lachesis mutus 30X, Moschus 12X, Pulsatilla 30X, 1 g each in 10 g.

Purpose

Relieves nervous exhaustion, anguish and anxiety, discomfort associated with PMS

Uses

For the temporary relief of:

- Nervous exhaustion
- Anguish and anxiety
- Discomfort associated with PMS

Warnings

Stop use and ask a doctor if symptoms persist, get worse, or if new symptoms occur.

PREGNANCY OR BREAST FEEDING

If pregnant or breastfeeding, ask a health care professional before use.

Keep out of reach of children.

Directions

Adults and children ≥ 12 years 5-10 drops 1-3 times daily in a little water or undiluted or as recommended.

Other information

- Tamper resistant: do not use if safety ring at base of cap is broken.
- Retain outer carton for full product information.

Inactive ingredients

Ethanol, purified water.

Questions?

Call 1-800-361-7872 or email questions@reckeweg.com

PACKAGE LABEL

NDC# 53346-1347-5

Dr. Reckeweg R47 Neuroglobin

Homeopathic preparation for the temporary relief of:

- Nervous exhaustion
- Anguish and anxiety
- Discomfort associated with PMS

Manufactured by:

Dr. Reckeweg Co. GmbH

D-64625 Bensheim

Germany

1.68 fl oz
(50 ml)